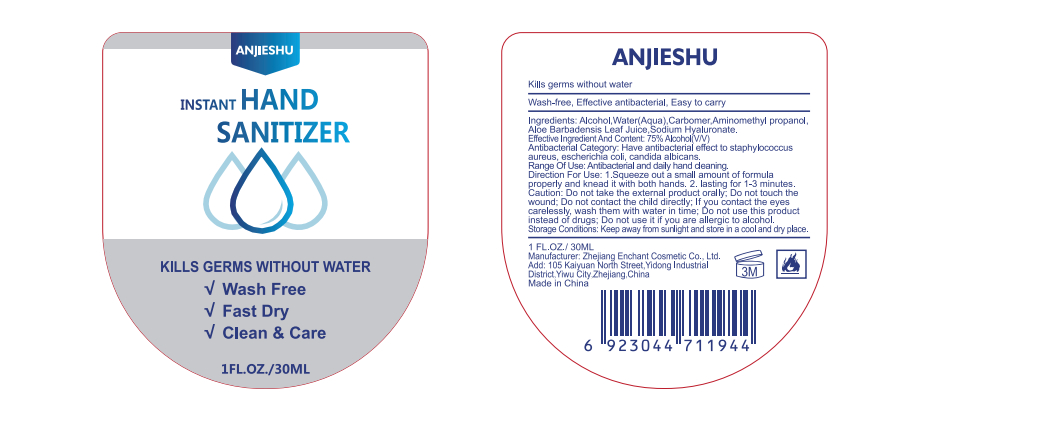 DRUG LABEL: Anjieshu Instant Hand Sanitizer
NDC: 52728-007 | Form: GEL
Manufacturer: Zhejiang Enchant Cosmetic Co., Ltd.
Category: otc | Type: HUMAN OTC DRUG LABEL
Date: 20200420

ACTIVE INGREDIENTS: ALCOHOL 22.5 mL/30 mL
INACTIVE INGREDIENTS: WATER; AMINOMETHYLPROPANOL; HYALURONATE SODIUM; CARBOMER HOMOPOLYMER, UNSPECIFIED TYPE

DOSAGE AND ADMINISTRATION

Storage Conditions. Keep away from sunlight and store in a cool and dry place.

PURPOSE

Disinfection
Sterilization
No Rinseing

ACTIVE INGREDIENT

alcohol

INDICATIONS AND USAGE

Range Of Use: Antibacterial and daily hand cleaning.

Direction For Use: 1. Squeeze out a small amount of formula properly and knead it with both hands.
2. lasting for 1-3 minutes.

INACTIVE INGREDIENT

Water(Aqua),Carbomer,Aminomethyl propanol,Aloe Barbadensis Leaf Juice,Sodium Hyaluronate.

WARNINGS

Caution: Do not take the external product orally; Do not touch the wound; Do not contact the child directly, If you contact the eyes carelessly, wash them with water in time; DO not use this product instead of drugs; Do not use it if you are allergic to alcohol.

keep out of reach of children